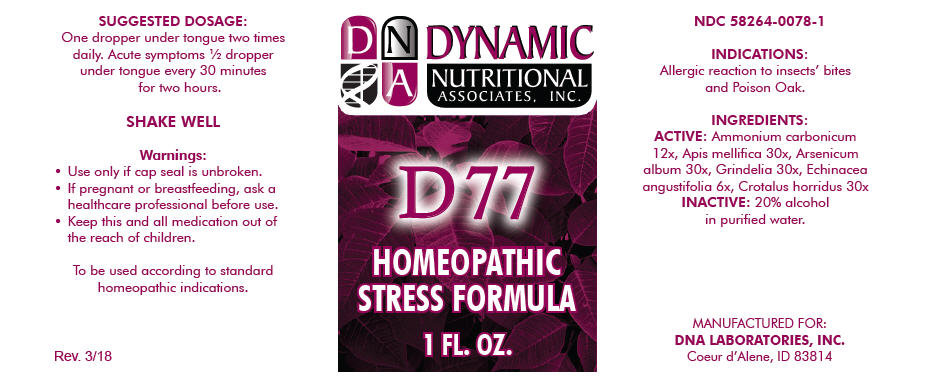 DRUG LABEL: D-77
NDC: 58264-0078 | Form: SOLUTION
Manufacturer: DNA Labs, Inc.
Category: homeopathic | Type: HUMAN OTC DRUG LABEL
Date: 20250113

ACTIVE INGREDIENTS: AMMONIUM CARBONATE 12 [hp_X]/1 mL; APIS MELLIFERA 30 [hp_X]/1 mL; ARSENIC TRIOXIDE 30 [hp_X]/1 mL; GRINDELIA HIRSUTULA FLOWERING TOP 30 [hp_X]/1 mL; ECHINACEA ANGUSTIFOLIA 6 [hp_X]/1 mL; CROTALUS HORRIDUS HORRIDUS VENOM 30 [hp_X]/1 mL
INACTIVE INGREDIENTS: ALCOHOL; WATER

D-77

NDC 58264-0078-1

INDICATIONS

PURPOSE

Allergic reaction to insects' bites and Poison Oak.

INGREDIENTS

ACTIVE

Ammonium carbonicum 12x, Apis mellifica 30x, Arsenicum album 30x, Grindelia 30x, Echinacea angustifolia 6x, Crotalus horridus 30x

INACTIVE

20% alcohol in purified water.

SUGGESTED DOSAGE

One dropper under tongue two times daily. Acute symptoms ½ dropper under tongue every 30 minutes for two hours.

STORAGE AND HANDLING

SHAKE WELL

Warnings

- Use only if cap seal is unbroken.

PREGNANCY OR BREAST FEEDING

- If pregnant or breastfeeding, ask a healthcare professional before use.

KEEP OUT OF REACH OF CHILDREN

- Keep this and all medication out of the reach of children.

To be used according to standard homeopathic indications.

PRINCIPAL DISPLAY PANEL - 1 FL. OZ. Bottle Label

DYNAMIC
NUTRITIONAL
ASSOCIATES, INC.

D 77

HOMEOPATHIC
STRESS FORMULA

1 FL. OZ.